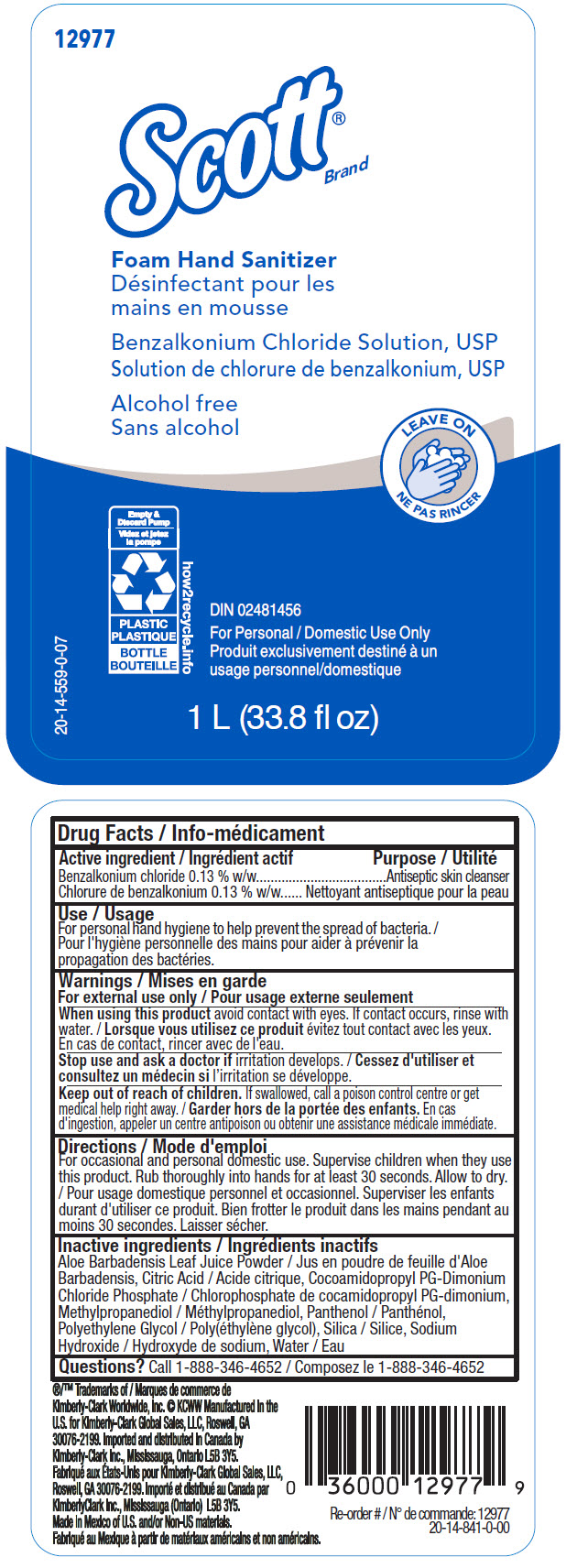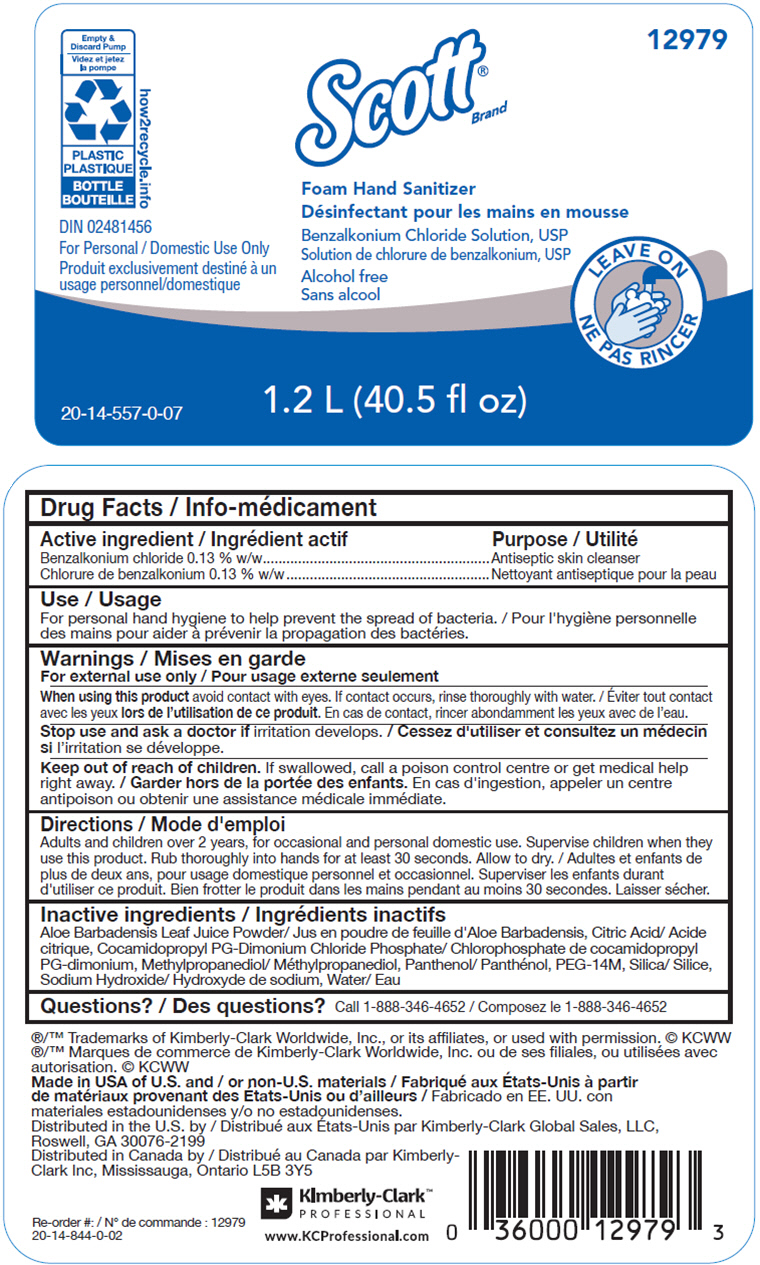 DRUG LABEL: SCOTT FOAM HAND SANITIZER
NDC: 55118-664 | Form: SOLUTION
Manufacturer: Kimberly-Clark
Category: otc | Type: HUMAN OTC DRUG LABEL
Date: 20250904

ACTIVE INGREDIENTS: Benzalkonium Chloride 1.3 mg/1000 mL
INACTIVE INGREDIENTS: ALOE VERA LEAF; CITRIC ACID MONOHYDRATE; COCAMIDOPROPYL PROPYLENE GLYCOL-DIMONIUM CHLORIDE PHOSPHATE; METHYLPROPANEDIOL; PANTHENOL; POLYETHYLENE OXIDE 600000; SILICON DIOXIDE; Sodium Hydroxide; WATER

SCOTT® FOAM HAND SANITIZER

Drug Facts

Active ingredient

Benzalkonium chloride 0.13 % w/w

Purpose

Antiseptic skin cleanser

Use

For personal hand hygiene to help prevent the spread of bacteria

Warnings

For external use only

When using this product avoid contact with eyes. If contact occurs, rinse with water.

Stop use and ask a doctor if irritation develops.

Keep out of reach of children. If swallowed, call a poison control centre or get medical help right away.

Directions

For occasional and personal domestic use. Supervise children when they use this product. Rub thoroughly into hands for at least 30 seconds. Allow to dry.

Inactive ingredients

Aloe Barbadensis Leaf Juice Powder, Citric Acid, Cocoamidopropyl PG-Dimonium Chloride Phosphate, Methylpropanediol, Panthenol, Polyethylene Glycol, Silica, Sodium Hydroxide, Water

Questions?

Call 1-888-346-4652

Imported and distributed in Canada by
Kimberly-Clark Inc., Mississauga, Ontario L5B 3Y5

PRINCIPAL DISPLAY PANEL - 1 L Bottle Label

12977

Scott®
Brand

Foam Hand Sanitizer

Benzalkonium Chloride Solution, USP

Alcohol free

LEAVE ON

Empty &
Discard Pump
PLASTIC
BOTTLE
how2recycle.info

DIN 02481456

For Personal / Domestic Use Only

20-14-559-0-07

1 L (33.8 fl oz)

PRINCIPAL DISPLAY PANEL - 1.2 L Bottle Label

12979

Scott®
Brand

Foam Hand Sanitizer

Benzalkonium Chloride Solution, USP

Alcohol free

LEAVE ON

Empty &
Discard Pump
PLASTIC
BOTTLE
how2recycle.info

DIN 02481456

For Personal / Domestic Use Only

20-14-557-0-07

1.2 L (40.5 fl oz)